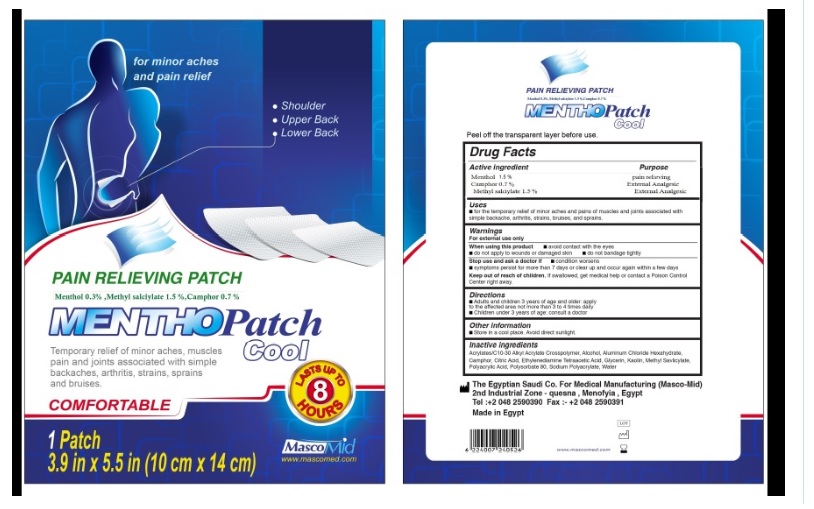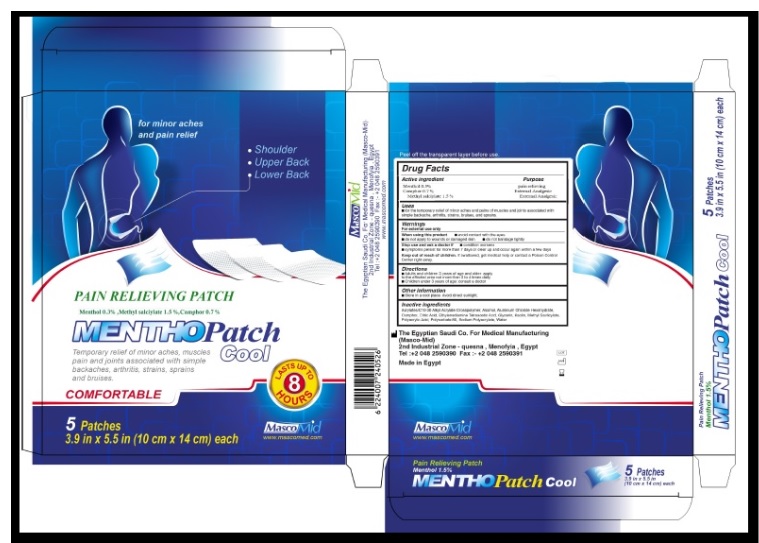 DRUG LABEL: Mentho patch
NDC: 72602-002 | Form: PATCH
Manufacturer: THE EGYPTIAN SAUDI CO FOR MEDICAL MANUFACTURING  MASCOMID
Category: otc | Type: HUMAN OTC DRUG LABEL
Date: 20251006

ACTIVE INGREDIENTS: MENTHOL 15 mg/1 g
INACTIVE INGREDIENTS: GLYCERIN; SODIUM POLYACRYLATE (2500000 MW); ALUMINUM CHLORIDE ANHYDROUS; CITRIC ACID MONOHYDRATE; TARTARIC ACID; POLYSORBATE 80; ISOPROPYL MYRISTATE; CARBOXYMETHYLCELLULOSE SODIUM (0.9 CARBOXYMETHYL SUBSTITUTION PER SACCHARIDE; 600 MPA.S AT 2%); EDETATE DISODIUM; POLYACRYLIC ACID (800000 MW); TITANIUM DIOXIDE; WATER; CARBOMER COPOLYMER TYPE B (ALLYL PENTAERYTHRITOL CROSSLINKED)

Menthopatch Cool

Purpose

For the temprorary releif of minor aches and pains of musceles and joints associated with simple backache, arthritis,strainsand sprains

Warnings

- FOR EXTERNAL USE ONLY
- When Using this Product
- Avoid contact with eyes
- Do not apply to open wounds, or to damaged skin
- Do not bandage tightly.

Directions

- Adults and children 3 years of age and older: apply to affected area not more than 3 to 4 times daily.
- Children under 3 years of age: consult doctor.

Stop use and ask doctor

- If condition worsens
- If symptoms persist more than 7 days or clear up and occur again with a few days

storage

- store in cool dry place avoid direct sunlight.

KEEP OUT OF REACH OF CHILDREN

If swallowed, get medical help or contact a Poison Control Center right away

Active ingridient section

Menthol,Camphor,Methyl salicylate

INACTIVE INGREDIENT SECTION

Glycerin ,Sodium poly acryl ate ,Aluminum chloride hex hydrate 2 ,
Anhydrous citric acid ,Tartaric acid 1 ,Poly sorbate -80 (tween 80) 0.5 ,Isopropyl myristate alcohol 2.5 ,Car boxy methyl cellulose (CMC) 2
EDETA 0.5 ,Polyvinyl pyrolidone(PVP-K90) 3 ,Water 48.35 ,titanium dioxide 0.05,ACRYLATE/ C10-30 ALKYL ACRYLATE,cross polymer